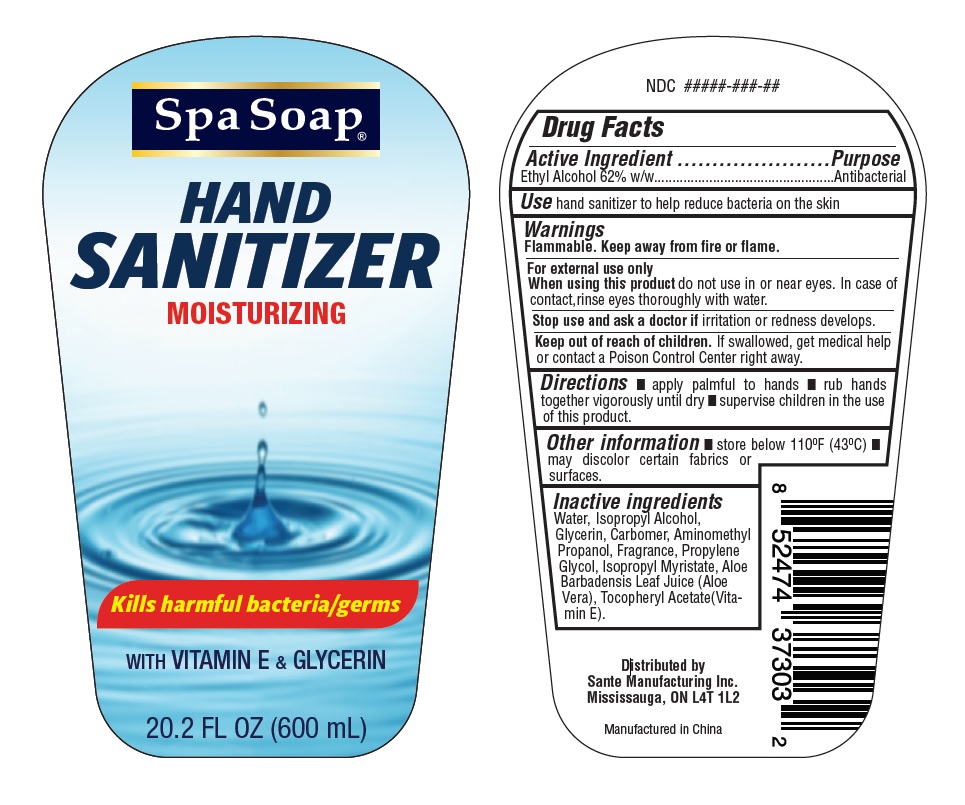 DRUG LABEL: Hand Sanitizer
NDC: 71020-101 | Form: GEL
Manufacturer: Sante Manufacturing Inc
Category: otc | Type: HUMAN OTC DRUG LABEL
Date: 20200617

ACTIVE INGREDIENTS: ALCOHOL 62 mL/100 mL
INACTIVE INGREDIENTS: CARBOMER COPOLYMER TYPE A; GLYCERIN; PROPYLENE GLYCOL; .ALPHA.-TOCOPHEROL ACETATE; AMINOMETHYLPROPANOL; ISOPROPYL MYRISTATE; ALOE; ISOPROPYL ALCOHOL; WATER

Spa Soap Hand Sanitizer

Active Ingredient

Ethyl alcohol 62%.

Purpose

Antiseptic

INDICATIONS AND USAGE

For handwashing to decrease bacteria on the skin.

Warnings

Flammable, keep away from fire or flame. For external use only.

When using this product Avoid contact with eyes. In case of contact flush eyes with water.

Stop use and ask a doctor If redness or irritation develop and persist for more than 72 hours.

Keep out of reach of children. If swallowed get medical help or contact a Poison Control Center right away.

Directions

Spread on both hands, rub in, let dry.

INACTIVE INGREDIENT

Inactive Ingredients: Water, Isopropyl Alcohol, Glycerin, Carbomer, Aminomethyl Propanol, Fragrance, Propylene Glycol, Isopropyl Myristate, Aloe Barbadensis Leaf Juice (Aloe Vera) Tocopheryl Acetate (Vitamin E)